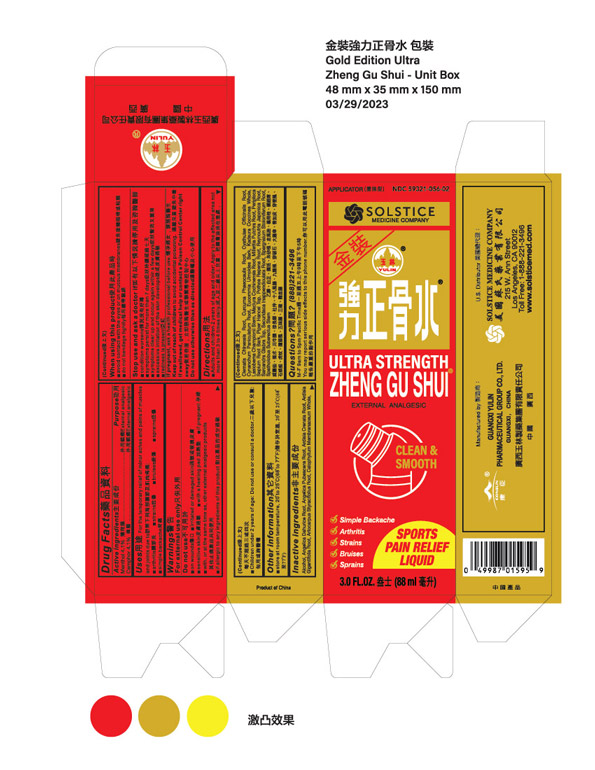 DRUG LABEL: ULTRA STRENGTH ZHENG GU SHUI
NDC: 59321-056 | Form: LINIMENT
Manufacturer: GUANGXI YULIN PHARMACEUTICAL GROUP CO LTD
Category: otc | Type: HUMAN OTC DRUG LABEL
Date: 20250714

ACTIVE INGREDIENTS: CAMPHOR (SYNTHETIC) 4.1 g/100 mL; MENTHOL 4.1 g/100 mL
INACTIVE INGREDIENTS: REYNOUTRIA JAPONICA ROOT; SECURIDACA INAPPENDICULATA ROOT; PIPER HANCEI TOP; ANGELICA PUBESCENS ROOT; CALOPHYLLUM MEMBRANACEUM WHOLE; PERIPLOCA SEPIUM ROOT BARK; ARDISIA CRENATA ROOT; CYATHULA OFFICINALIS ROOT; CYNANCHUM PANICULATUM ROOT; KADSURA COCCINEA WHOLE; MACLURA COCHINCHINENSIS ROOT; CLEMATIS CHINENSIS ROOT; ALCOHOL; ARTOCARPUS STYRACIFOLIUS ROOT; CURCUMA PHAEOCAULIS ROOT; EUCOMMIA ULMOIDES BARK; LASIOBEMA CHAMPIONII STEM; MILLETTIA PULCHRA ROOT; POTHOS REPENS ROOT; SARCANDRA GLABRA TOP; SPARGANIUM STOLONIFERUM ROOT; SPATHOLOBUS SUBERECTUS STEM; ANGELICA DAHURICA ROOT; ARDISIA GIGANTIFOLIA ROOT

Active ingredient
Menthol 4.1%
Camphor 4.1%

Purpose
External analgesic
External analgesic

Uses
For the temporary relief of minor aches and pains of muscles and joints due to:
■ arthritis
■ strains
■ bruises
■ sprains
■ simple backache

Warnings
For external use only

Do not use
■ on wounds
■ on irritated or damaged skin
■ sensitive skin
■ with a heating pad
■ if pregnant
■ with, or at the same time as, other external analgesic products
■ if allergic to any ingredients of this product

When using this product
■ avoid contact with the eyes or mucous membranes
■ do not bandage tightly

Stop use and ask a doctor if
■ condition worsens
■ symptoms persist for more than 7 days
■ symptoms clear up and occur again within a few days
■ excessive irritation of the skin develops
■ redness is present

PREGNANCY OR BREAST FEEDING

If pregnant, ask a health professional before use.

Keep out of reach of children to avoid accidental poisoning.

If swallowed, get medical hep or contact a Poison Control Center right away.

Do not use otherwise than as directed.

ADVERSE REACTIONS

Report any unexpected side effects from the use of this product to the FDA MedWatch Program.

Directions
■ Adults and children 2 years of age and older: Apply to affected area not more than 3 to 4 times daily.
■ Children under 2 years of age: do no use or consult a doctor.

Other information
■ store at room temperature, 20 to 25 C (68 to 77 F)

INACTIVE INGREDIENT

Inactive ingredients Alcohol, angelica dahurice root, angelica pubescens root, ardisia crenata root, ardisia gigantifolia root, artocarpus styracifolius root, calophyllum membranaceum whole, clematis chinensis root, curcuma phaeocaulis root, cyathulae officinalis root, cynanchum paniculatum root, eucommia ulmoides bark, kadsura coccinea whole, lasiobema championii stem, maclura cochinensis root, millettia pulchra root, periploca sepium root bark, piper hancei top, pothos repens root, reynoutria japonica root, sarcandra glabra top, securidaca inappendiculata root, spargnaium stoloniferum root, and spatholobus suberectus stem.

Questions or comments? (888) 221-3496 M-F 9 am to 5 pm
■ You may also report serious side effects to this phone number

PACKAGE LABEL

ULTRA STRENGTH ZHENG GU SHUI

MENTHOL AND CAMPHOR

NDC 59321-056-02

EXTERNAL ANALGESIC

3.0 FL OZ (88 ML)